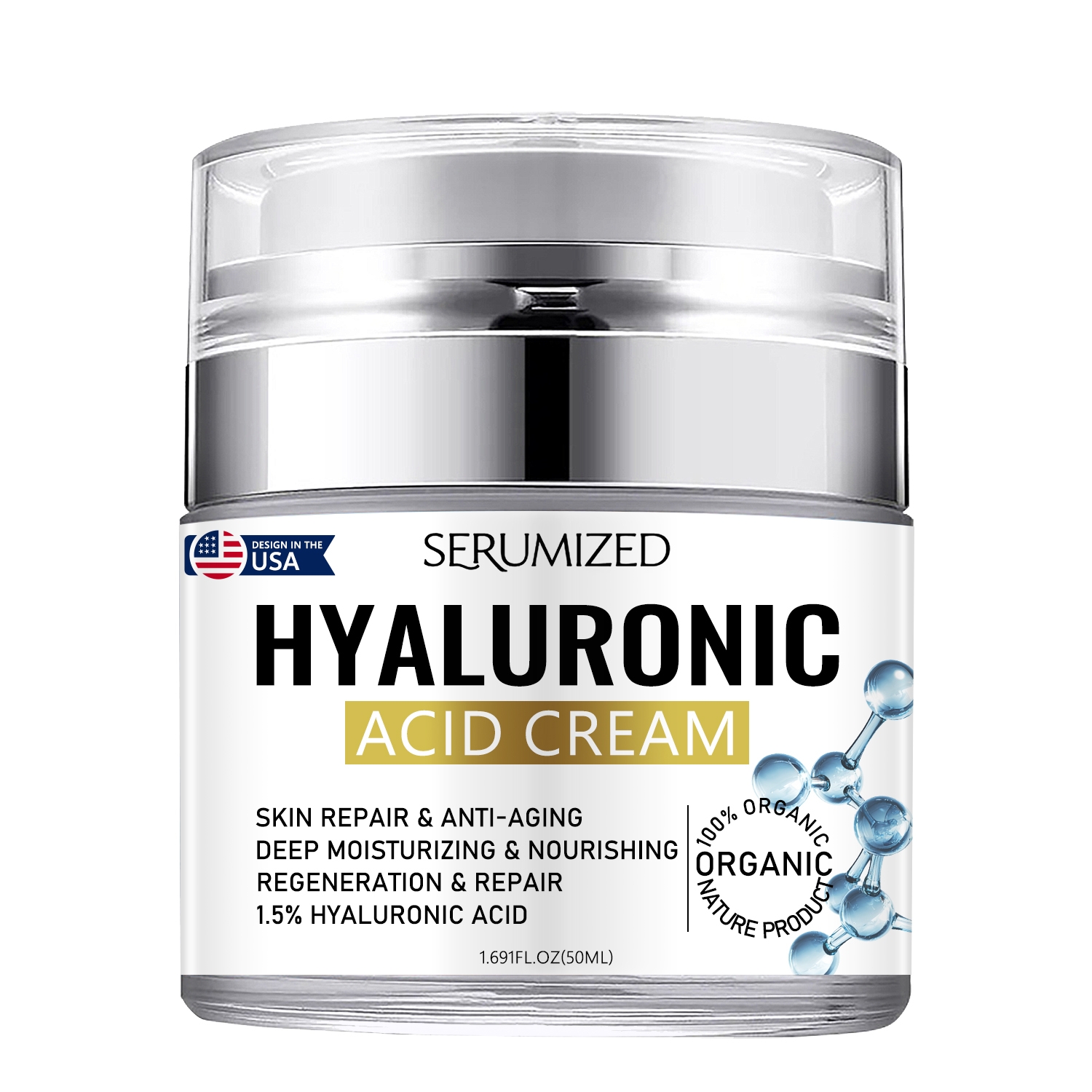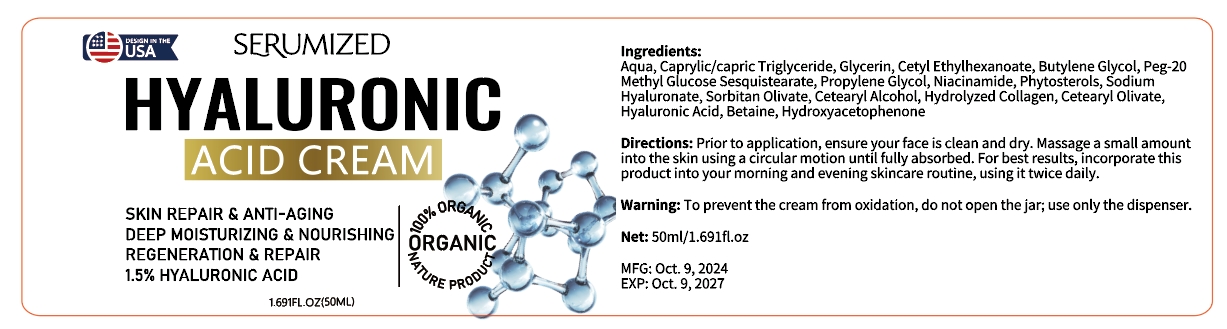 DRUG LABEL: hyaluronic acid cream
NDC: 84025-290 | Form: CREAM
Manufacturer: Guangzhou Yanxi Biotechnology Co., Ltd
Category: otc | Type: HUMAN OTC DRUG LABEL
Date: 20241220

ACTIVE INGREDIENTS: CAPRYLIC/CAPRIC TRIGLYCERIDE 3 mg/50 mL; GLYCERIN 5 mg/50 mL
INACTIVE INGREDIENTS: WATER

DOSAGE AND ADMINISTRATION

Prior to application, ensure your face is clean and dry. Massage a small amount into the skin using a circular motion until fully absorbed.

WARNINGS

Keep out of children

INACTIVE INGREDIENT

Aqua

INDICATIONS AND USAGE

For daily skin care

Keep out of children

PURPOSE

Deep moisturizing and nourishing